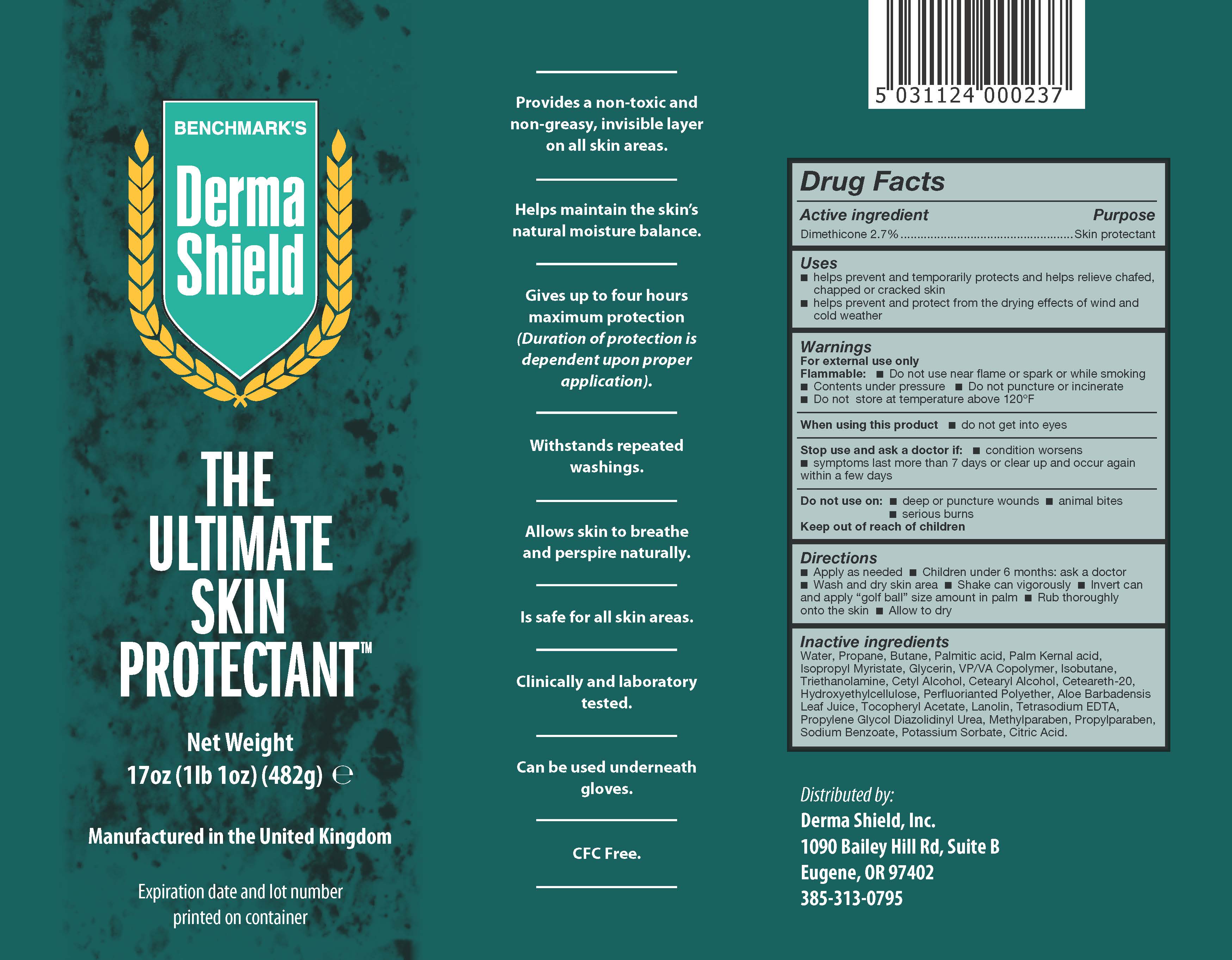 DRUG LABEL: Ultimate Skin Protectant Derma Shield
NDC: 70233-010 | Form: AEROSOL
Manufacturer: Fleet Laboratories LTD
Category: otc | Type: HUMAN OTC DRUG LABEL
Date: 20191004

ACTIVE INGREDIENTS: DIMETHICONE 2.7 g/100 g
INACTIVE INGREDIENTS: .ALPHA.-TOCOPHEROL ACETATE; ALOE VERA LEAF; ISOBUTANE; ISOPROPYL MYRISTATE; EDETATE SODIUM; LANOLIN; POLYOXYL 20 CETOSTEARYL ETHER; PALM KERNEL ACID; COPOVIDONE K25-31; PROPYLPARABEN; CITRIC ACID MONOHYDRATE; DIAZOLIDINYL UREA; GLYCERIN; HYDROXYETHYL CELLULOSE (4000 MPA.S AT 1%); METHYLPARABEN; PROPYLENE GLYCOL; SODIUM BENZOATE; PALMITIC ACID; CETOSTEARYL ALCOHOL; TROLAMINE; WATER; CETYL ALCOHOL; PERFLUOROPOLYMETHYLISOPROPYL ETHER; POTASSIUM SORBATE; PROPANE; BUTANE

Ultimate Skin Protectant Derma Shield

Active ingredient Purpose

Dimethicone 2.7% Skin Protectant

Uses

- Helps prevent and temporarily protects and helps relieve chafed, chapped or cracked skin
- Helps prevent and protect from the drying effects of wind and cold weather

Keep out of reach of children

Stop use and ask a doctor if:

- condition worsens
- symptoms last more than 7 days or clear up again within a few days

Warnings

For external use only

Flammable:

- Do not use near flame or spark or while smoking
- Contents under pressure
- Do not puncture or incinerate
- Do not store at temperature above 120°F

Directions

- Apply as needed
- Children under 6 months: ask a doctor
- Wash and dry skin area
- Shake can vigourously
  - Invert can and apply "golf Ball" size amount in palm
  - Rub thoroughly onto the skin
  - Allow to dry

INACTIVE INGREDIENT

Inactive ingredients Water, Propane, Butane, Palmitic acid, Palm Kernal acid, Isopropyl Myristate, Glycerin, VP/VA Copolymer, Isobutane, Triethanolamine, Cetyl Alcohol, Cetearyl Alcohol, Ceteareth-20, Hydroxyethylcellulose, Perfluorianted Polyether, Aloe Barbadensis Leaf Juice, Tocopheryl Acetate, Lanolin, Tetrasodium EDTA, Propylene Glycol Diazolidinyl Urea, Methylparaben, Propylparaben, Sodium Benzoate, Potassium Sorbate,Citric Acid.

PACKAGE LABEL

Benchmark's

DermaShield

The Ultimate Skin Protectant

Net Weight 17 oz(1lb 1 oz) (482g)